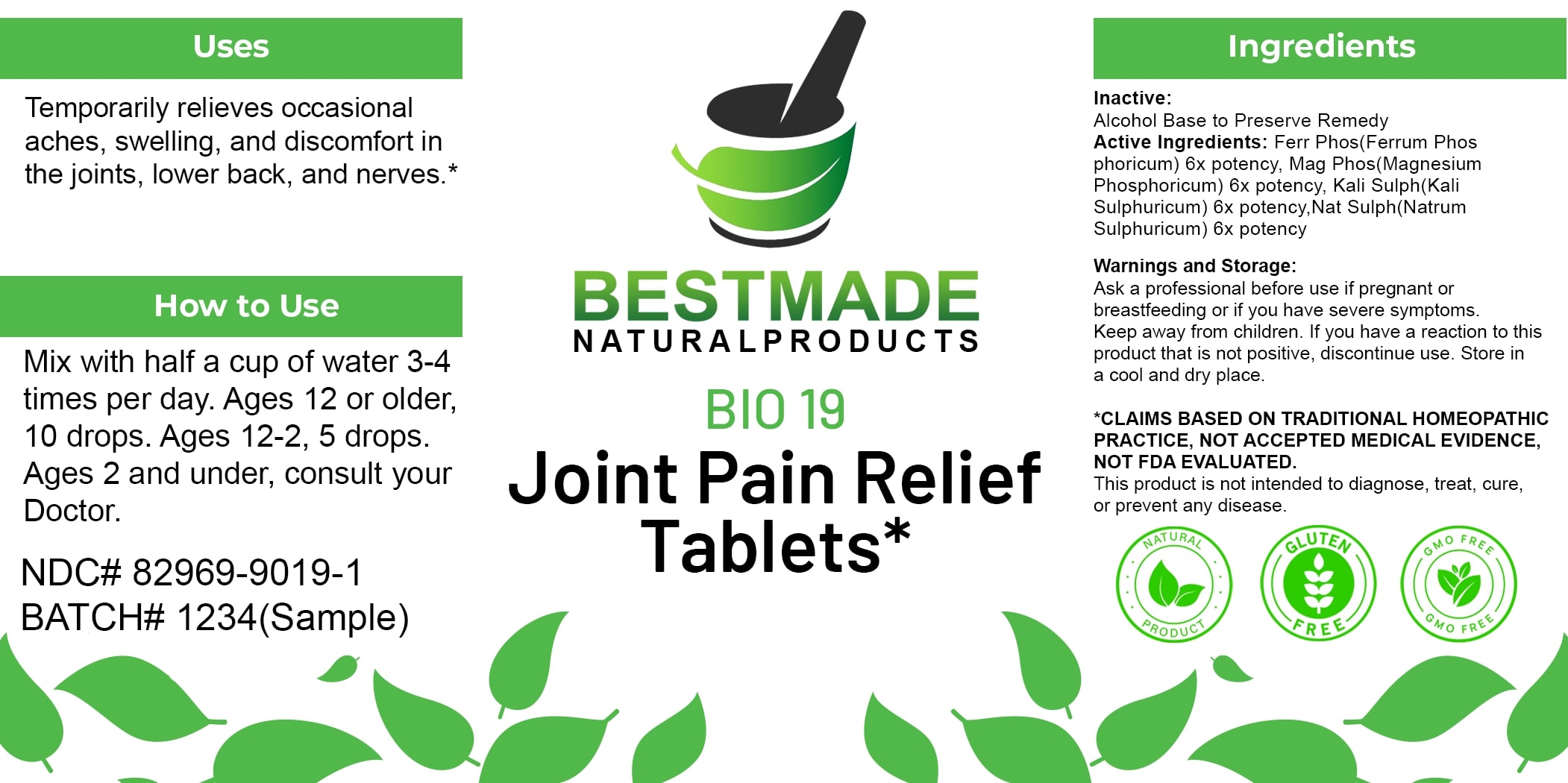 DRUG LABEL: Bestmade Natural Products BIO19
NDC: 82969-9019 | Form: LIQUID
Manufacturer: Bestmade Natural Products
Category: homeopathic | Type: HUMAN OTC DRUG LABEL
Date: 20250311

ACTIVE INGREDIENTS: MAGNESIUM PHOSPHATE, DIBASIC TRIHYDRATE 6 [hp_X]/6 [hp_X]; SODIUM SULFATE 6 [hp_X]/6 [hp_X]; POTASSIUM SULFATE 6 [hp_X]/6 [hp_X]; FERROSOFERRIC PHOSPHATE 6 [hp_X]/6 [hp_X]
INACTIVE INGREDIENTS: ALCOHOL 6 [hp_X]/6 [hp_X]

BIO 19 Joint Pain Relief Tablets*

DOSAGE AND ADMINISTRATION

How to Use

Mix with half a cup of water 3-4 times per day. Ages 12 or older, 10 drops. Ages 12-2, 5 drops. Ages 2 and under, consult your Doctor.

INACTIVE INGREDIENT

Ingredients

Inactive: Alcohol Base to Preserve Remedy

ACTIVE INGREDIENT

Active Ingredients: Ferr Phos(Ferrum Phosphoricum) 6x potency, Mag Phos(Magnesium Phosphoricum) 6x potency, Kali Sulph(Kali Sulphuricum) 6x potency, Nat Sulph(Natrum Sulphuricum) 6x potency

Uses

Temporarily relieves occasional aches, swelling, and discomfort in the joints, lower back, and nerves.*

*CLAIMS BASED ON TRADITIONAL HOMEOPATHIC PRACTICE, NOT ACCEPTED MEDICAL EVIDENCE. NOT FDA EVALUATED.

This product is not intended to diagnose, treat, cure, or prevent any disease.

Uses

Temporarily relieves occasional aches, swelling, and discomfort in the joints, lower back, and nerves.*

*CLAIMS BASED ON TRADITIONAL HOMEOPATHIC PRACTICE, NOT ACCEPTED MEDICAL EVIDENCE. NOT FDA EVALUATED.

This product is not intended to diagnose, treat, cure, or prevent any disease.

KEEP OUT OF REACH OF CHILDREN

Warnings and Storage:

Ask a professional before use if pregnant or breastfeeding or if you have severe symptoms. Keep away from children. If you have a reaction to this product that is not positive, discontinue use. Store in a cool and dry place.

Warnings and Storage:

Ask a professional before use if pregnant or breastfeeding or if you have severe symptoms. Keep away from children. If you have a reaction to this product that is not positive, discontinue use. Store in a cool and dry place.

*CLAIMS BASED ON TRADITIONAL HOMEOPATHIC PRACTICE, NOT ACCEPTED MEDICAL EVIDENCE. NOT FDA EVALUATED.

This product is not intended to diagnose, treat, cure, or prevent any disease.

Entire package label